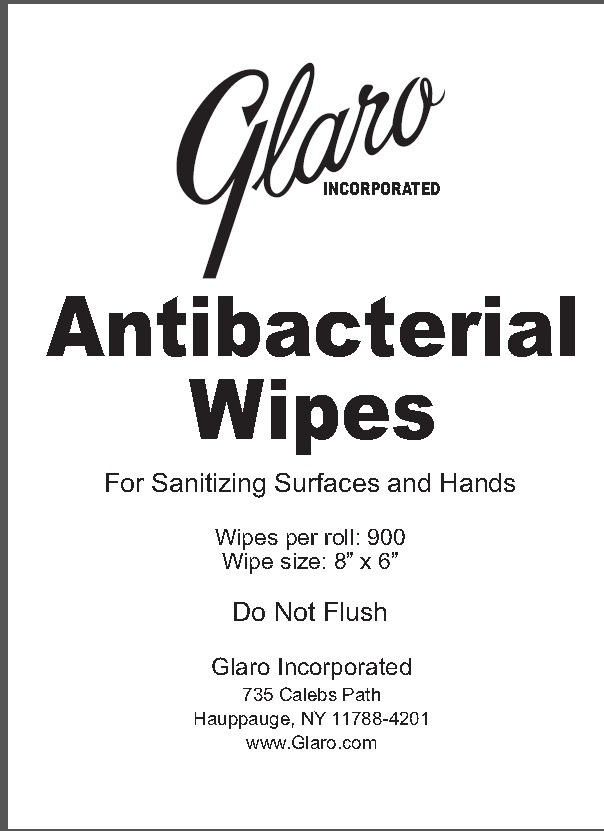 DRUG LABEL: Antibacterial Wipes
NDC: 70691-900 | Form: SWAB
Manufacturer: Glaro, Incorporated
Category: otc | Type: HUMAN OTC DRUG LABEL
Date: 20231106

ACTIVE INGREDIENTS: BENZALKONIUM CHLORIDE 0.13 g/100 g
INACTIVE INGREDIENTS: WATER; PHENOXYETHANOL; DECYL GLUCOSIDE; POTASSIUM SORBATE; SODIUM BENZOATE; EDETATE DISODIUM; CITRIC ACID MONOHYDRATE; ALOE VERA LEAF

Drug Facts

Active ingredient

Benzalkonium chloride 0.13%

Purpose

Antimicrobial

Uses

- For hand sanitizing to decrease bacteria on the skin
- Recommended for repeated use
- For surface sanitizing

Warnings

For external use only

Do not use if

you are allergic to any of these ingredients

When using this product

avoid contact with eyes. In case of eye contact, flush eyes with water.

Stop use and ask a doctor

If irritation or redness develops, or if condition persists for more than 72 hours.

Keep out of reach of children

If swallowed, get medical help or contact a Poison Control Center immediately.

Directions

- Adults and Children 2 Years and Over. Apply to hands and face; Allow to dry without wiping.
- Children Under 2 Years: Ask a doctor before use.

To Dispense:

1. DO NOT remove wipes roll from the heat sealed plastic bag.
2. DO NOT cut across the top of the entire bag.
3. Cut a “V” shaped opening on the top center of the bag.
4. Pull up the first wipe from the center of the roll.
5. Thread through the star shaped opening in the underside of the dispenser cover.
6. Secure the cover to the body.
7. To dispense, pull each sheet up and slightly to the side.

Dispose of wipes in thrash. Do not flush

Other information

- Store below 95oF (35oC).
- Keep closed tightly.
- May discolor certain fabric or surfaces

Inactive ingredients

Water, SD Alcohol 40, Phenoxyethanol, Decyl Glucoside, Potassium Sorbate, Sodium Benzoate, Disodium EDTA, Citric Acid, Aloe Barbadensis (Aloe) Leaf Extract, Fragrance.

Principal Display Panel

NDC:70691-900-13

Glaro Incorporated

Antibacterial Wipes For Sanitizing Surfaces and Hands

Wipes per roll: 900

Wipe size: 8” x 6”

Do Not Flush

Glaro Incorporated 735 Calebs Path Hauppauge, NY 11788-4201

www.Glaro.com